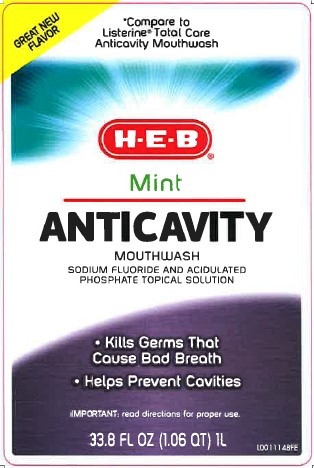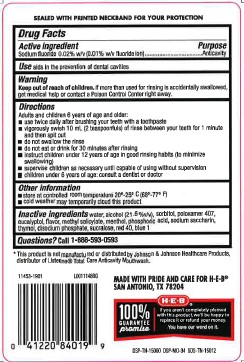 DRUG LABEL: Anticavity Fluoride Rinse
NDC: 37808-163 | Form: MOUTHWASH
Manufacturer: H E B
Category: otc | Type: HUMAN OTC DRUG LABEL
Date: 20260224

ACTIVE INGREDIENTS: SODIUM FLUORIDE 1 mg/1 mL
INACTIVE INGREDIENTS: WATER; ALCOHOL; SORBITOL; POLOXAMER 407; EUCALYPTOL; METHYL SALICYLATE; MENTHOL; PHOSPHORIC ACID; SACCHARIN SODIUM; THYMOL; SODIUM PHOSPHATE, DIBASIC, ANHYDROUS; SUCRALOSE; FD&C RED NO. 40; FD&C BLUE NO. 1

HEB 163.005/163AF
Anticavity Fluoride Rinse

Tamper Evident Statement

SEALED WITH PRINTED NECKBAND FOR YOUR PROTECTION

Active ingredient

Sodium fluoride 0.0221% (0.01% w/v fluoride ion)

Purpose

Anticavity

Use

aids in the prevention of dental cavities

Warnings

For this product

Keep out of reach of children.

If more than used for rinsing is accidentally swallowed, get medical help or contact a Poison Control Center right away.

Directions

Adults and children 6 years of age and older:

- use twice daily after brushing your teeth with toothpaste
- vigorously swish 10 mL (2 teaspoonfuls) of rinse between your teeth for 1 minute and then spit out
- do not swallow the rinse
- do not eat or drink for 30 minutes after rinsing
- instruct children under 12 years of age in good rinsing habits (to minimize swallowing)
- supervise children as necessary until capable of using without supervision
- children under 6 years of age: consult a dentist or doctor

Other information

- store at controlled room temperature 20⁰ -25⁰ C (68⁰ - 77⁰ F)
- cold weather may temporarily cloud this product

Inactive ingredients

water, alcohol (21.6 %v/v), sorbitol, poloxamer 407, eucalyptol, flavor, methyl salicylate, menthol, phosphoric acid, sodium saccharin, thymol, disodium phosphate, sucralose, red 40, blue 1

Questions?

Call 1-888-593-0593

Disclaimer

*This product is not manufacturd or distributed by Johnson & Johnson Healthcare Products, distributor of Listerine®Total Care Anticavity Mouthwash.

ADVERSE REACTION

MADE WITH PRIDE AND CARE FOR H-E-B®

SAN ANTONIO, TX 78204

H-E-B®100% GUARANTEE promise

If you aren't completely pleased with this product, we'll be happy to replace it or refund your money.

You have our word on it.

DSP-TN-15000 DSP-MO-34 SDS-TN-15012

principal display panel

GREAT NEW FLAVOR

*Compare to Listerine®Total Care Anticavity Mouthwash

H-E-B®

Mint

ANTICAVITY MOUTHWASH

SODIUM FLUORIDE AND ACIDULATED PHOSPHATE TOPICAL SOLUTION

- Kills Germs That Cause Bad Breath
- Helps Prevent Cavities

IMPORTANT: read directions for proper use.

33.8 FL OZ (1 QT) 1 L